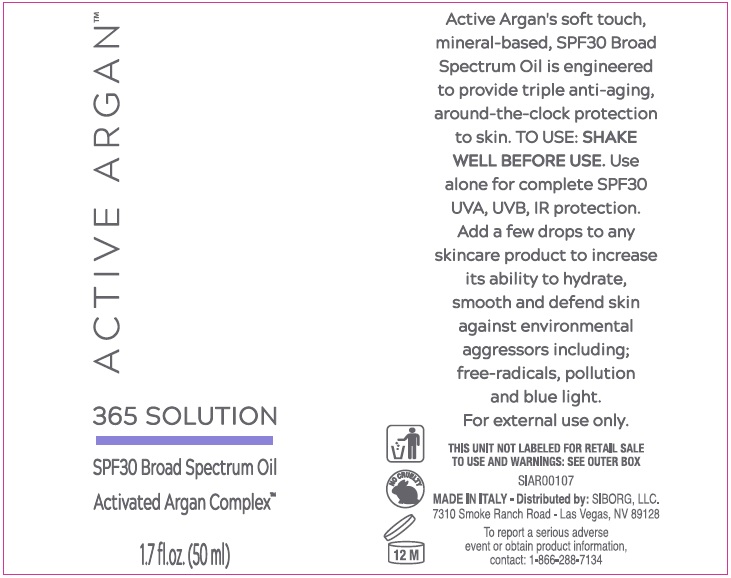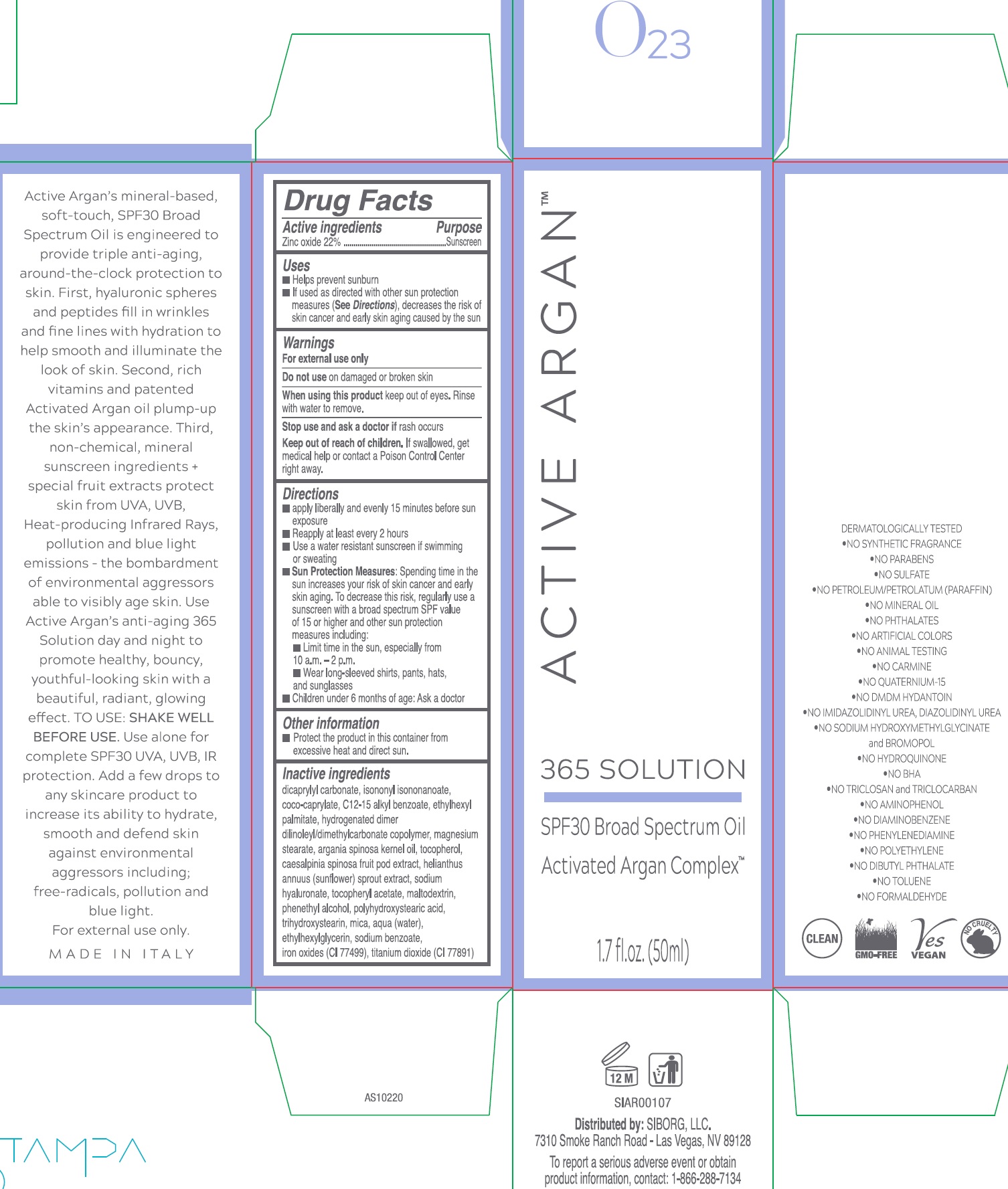 DRUG LABEL: ACTIVE ARGAN 365 SPF 30 BROAD SPECTRUM ACTIVATED ARGAN COMPLEX
NDC: 70803-250 | Form: OIL
Manufacturer: SIBORG LLC
Category: otc | Type: HUMAN OTC DRUG LABEL
Date: 20231212

ACTIVE INGREDIENTS: ZINC OXIDE 220 mg/1 mL
INACTIVE INGREDIENTS: DICAPRYLYL CARBONATE; ISONONYL ISONONANOATE; COCO-CAPRYLATE; ALKYL (C12-15) BENZOATE; ETHYLHEXYL PALMITATE; MAGNESIUM STEARATE; ARGAN OIL; TOCOPHEROL; CAESALPINIA SPINOSA FRUIT POD; HELIANTHUS ANNUUS SPROUT; HYALURONATE SODIUM; .ALPHA.-TOCOPHEROL ACETATE; MALTODEXTRIN; PHENYLETHYL ALCOHOL; TRIHYDROXYSTEARIN; MICA; WATER; ETHYLHEXYLGLYCERIN; SODIUM BENZOATE; FERRIC OXIDE RED; TITANIUM DIOXIDE

ACTIVE ARGAN 365 SOLUTION SPF 30 BROAD SPECTRUM OIL ACTIVATED ARGAN COMPLEX

Active ingredients

Zinc oxide 22%

Purpose

Sunscreen

Inactive Ingredients

dicaprylyl carbonate, isononyl isononanoate,
coco-caprylate, C12-15 alkyl benzoate, ethylhexyl
palmitate, hydrogenated dimer
dilinoleyl/dimethylcarbonate copolymer, magnesium
stearate, argania spinosa kernel oil, tocopherol,
caesalpinia spinosa fruit pod extract, helianthus
annuus (sunflower) sprout extract, sodium
hyaluronate, tocopheryl acetate, maltodextrin,
phenethyl alcohol, polyhydroxystearic acid,
trinydroxystearin, mica, aqua (water),
ethylhexylglycerin, sodium benzoate,
iron oxides (CI 77499), titanium dioxide (Cl 77891)

Uses

- Helps prevent sunburn
- If used as directed with other sun protection measures (), decreases the risk of skin cancer and early skin aging caused by the sun See Directions

Warnings

For external use only

Do not use

on damaged or broken skin

When using this product

keep out of eyes. Rinse with water to remove.

Stop use and ask a doctor if

rash occurs

Keep out of reach of children.

If swallowed, get medical help or contact a Poison Control Center right away.

Directions

- apply liberally and evenly 15 minutes before sun exposure
- Reapply at least every 2 hours
- Use a water resistant sunscreen if swimming or sweating
- Spending time in the sun increases your risk of skin cancer and early skin aging. To decrease this risk, regularly use a sunscreen with a broad spectrum SPF value of 15 or higher and other sun protection measures including: Sun Protection Measures:
- Limit time in the sun, especially from 10 a.m. - 2 p.m.
- Wear long-sleeved shirts, pants, hats and sunglasses
- Children under 6 months of age: Ask a doctor

Other information

dicaprylyl carbonate, isononyl isononanoate, coco-caprylate, C12-15 alkyl benzoate, ethylhexyl palmitate, hydrogenated dimer dilinoleyl/dimethylcarbonate copolymer, magnesium stearate, argania spinosa kernel oil, tocopherol, caesalpinia spinosa fruit pod extract, helianthus annuus (sunflower) sprout extract, sodium hyaluronate, tocopheryl acetate, maltodextrin, phenethyl alcohol, polyhydroxystearic acid, trihydroxystearin, mica, aqua (water), ethylhexylglycerin, sodium benzoate, iron oxides (CI 77499), titanium dioxide (CI 77891)